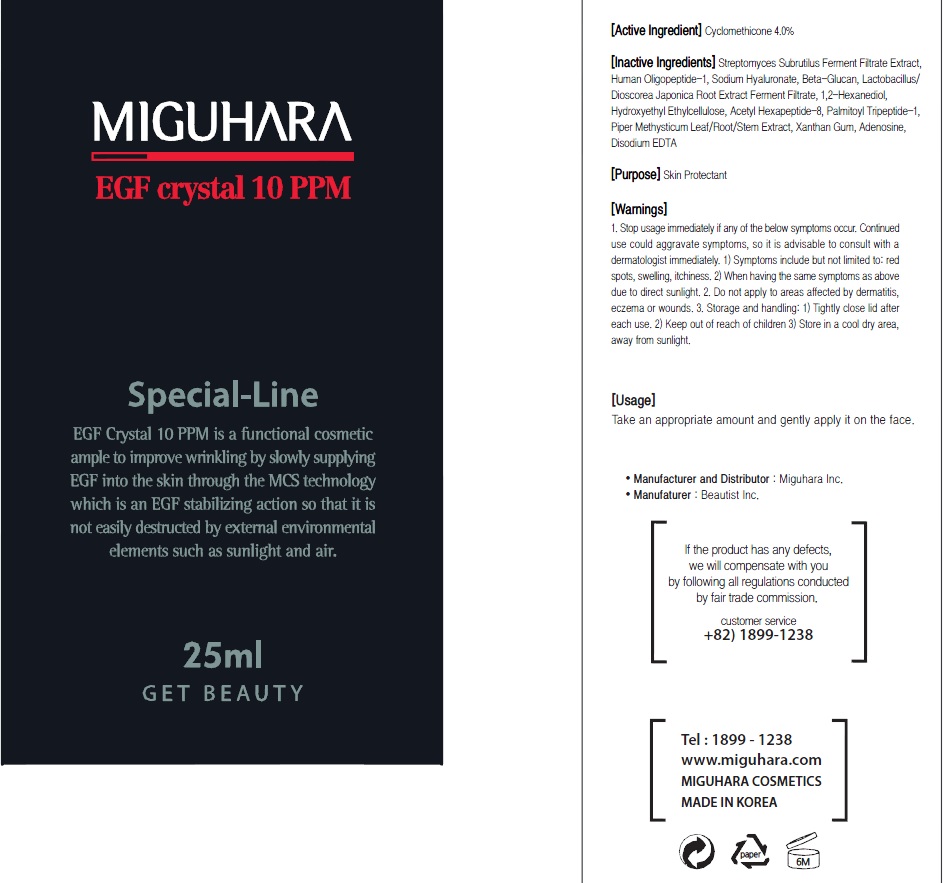 DRUG LABEL: EGF Crystal 10 ppm
NDC: 70380-180 | Form: CREAM
Manufacturer: MIGUHARA
Category: otc | Type: HUMAN OTC DRUG LABEL
Date: 20160222

ACTIVE INGREDIENTS: Glycerin 1.0 g/25 mL
INACTIVE INGREDIENTS: HYALURONATE SODIUM; 1,2-Hexanediol

ACTIVE INGREDIENT

Active Ingredient: Glycerin 4.0%

INACTIVE INGREDIENT

Inactive Ingredients: Streptomyces Subrutilus Ferment Filtrate Extract, Human Oligopeptide-1, Sodium Hyaluronate, Beta-Glucan, Lactobacillus/Dioscorea Japonica Root Extract Ferment Filtrate, 1,2-Hexanediol, Hydroxyethyl Ethylcellulose, Acetyl Hexapeptide-8, Palmitoyl Tripeptide-1, Piper Methysticum Leaf/Root/Stem Extract, Xanthan Gum, Adenosine, Disodium EDTA

PURPOSE

Purpose: Skin Protectant

WARNINGS

1. Stop usage immediately if any of the below symptoms occur. Continued use could aggravate symptoms, so it is advisable to consult with a dermatologist immediately. 1) Symptoms include but not limited to: red spots, swelling, itchiness. 2) When having the same symptoms as above due to direct sunlight. 2. Do not apply to areas affected by dermatitis, eczema or wounds. 3. Storage and handling: 1) Tightly close lid after each use. 2 Keep out of reach of children 3) Store in a cool dry area, away from sunlight

KEEP OUT OF REACH OF CHILDREN

Usage

Usage: Take an appropriate amount and gently apply it on the face.

Usage

Usage: Take an appropriate amount and gently apply it on the face.